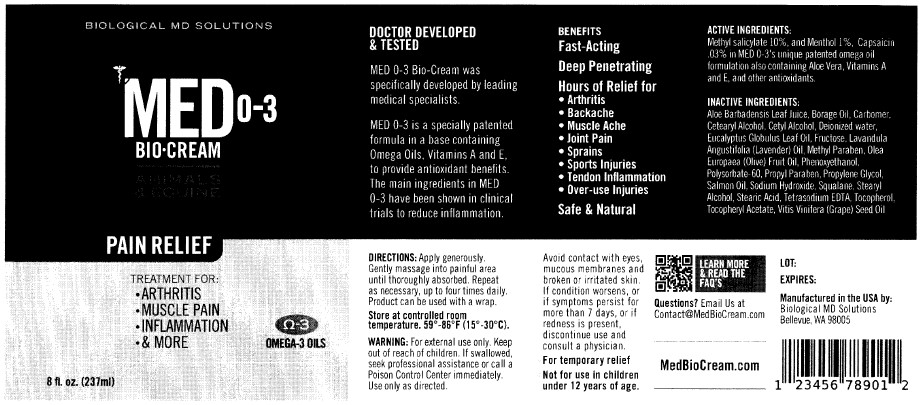 DRUG LABEL: MED O-3 BIO-
NDC: 83538-101 | Form: CREAM
Manufacturer: Biological M.D. Solutions LLC
Category: otc | Type: HUMAN OTC DRUG LABEL
Date: 20240106

ACTIVE INGREDIENTS: METHYL SALICYLATE 10 g/100 mL; CAPSAICIN 0.03 g/100 mL; MENTHOL 1 g/100 mL
INACTIVE INGREDIENTS: POLYSORBATE 60; PROPYLPARABEN; STEARIC ACID; BORAGE OIL; STEARYL ALCOHOL; EDETATE SODIUM; TOCOPHEROL; CETYL ALCOHOL; CETOSTEARYL ALCOHOL; WATER; EUCALYPTUS OIL; METHYLPARABEN; ATLANTIC SALMON OIL; SODIUM HYDROXIDE; OLIVE OIL; PHENOXYETHANOL; SQUALANE; FRUCTOSE; .ALPHA.-TOCOPHEROL ACETATE; GRAPE SEED OIL; CARBOMER HOMOPOLYMER, UNSPECIFIED TYPE; LAVENDER OIL; ALOE VERA LEAF; PROPYLENE GLYCOL

BIOLOGICAL MD SOLUTIONS (as PLD) - Med O-3 Bio-Cream (83538-101)

ACTIVE INGREDIENTS

METHYL SALICYLATE 10%

MENTHOL 1%

CAPSAICIN 0.03%

PURPOSE

TOPICAL ANALGESIC

USES

FAST ACTING

DEEP PENETRATING

HOURS OF RELIEF FOR

- ARTHRITIS
- BACKACHE
- MUSCLE ACHE
- JOINT PAIN
- SPRAINS
- SPORTS INJURIES
- TENDON INFLAMMATION
- OVER-USE INJURIES

WARNINGS

FOR EXTERNAL USE ONLY.

AVOID CONTACT WITH EYES, MUCOUS MEMBRANES AND BROKEN OR IRRITATED SKIN. IF CONDITION WORSENS, OR IF SYMPTOMS PERSIST FOR MORE THAN 7 DAYS, OR IF REDNESS IS PRESENT, DISCONTINUE USE AND CONSULT A PHYSICIAN.

FOR TEMPORARY RELIEF.

NOT FOR USE IN CHILDREN UNDER 12 YEARS OF AGE.

KEEP OUT OF REACH OF CHILDREN. IF SWALLOWED, SEEK PROFESSIONAL ASSISTANCE OR CALL A POISON CONTROL CENTER IMMEDIATELY. USE ONLY AS DIRECTED.

DIRECTIONS

APPLY GENEROUSLY. GENTLY MASSAGE INTO PAINFUL AREA UNTIL THOROUGHLY ABSORBED. REPEAT AS NECESSARY, UP TO FOUR TIMES DAILY. PRODUCT CAN BE USED WITH A WRAP.

STORAGE AND HANDLING

STORE AT CONTROLLED ROOM TEMPERATURE. 59° - 86°F (15° - 30°C).

INACTIVE INGREDIENTS

ALOE BARBADENSIS LEAF JUICE, BORAGE OIL, CARBOMER, CETEARYL ALCOHOL, CETYL ALCOHOL, DEIONIZED WATER, EUCALYPTUS GLOBULUS LEAF OIL, FRUCTOSE, LAVANDULA ANGUSTIFOLIA (LAVENDER) OIL, METHYL PARABEN, OLEA EUROPAEA (OLIVE) FRUIT OIL, PHENOXYETHANOL, POLYSORBATE-60, PROPYL PARABEN, PROPYLENE GLYCOL, SALMON OIL, SODIUM HYDROXIDE, SQUALANE, STEARYL ALCOHOL, STEARIC ACID, TETRASODIUM EDTA, TOCOPHEROL, TOCOPHERYL ACETATE, VITIS VINIFERA (GRAPE) SEED OIL

QUESTIONS?

EMAIL US AT CONTACT@MEDBIOCREAM.COM